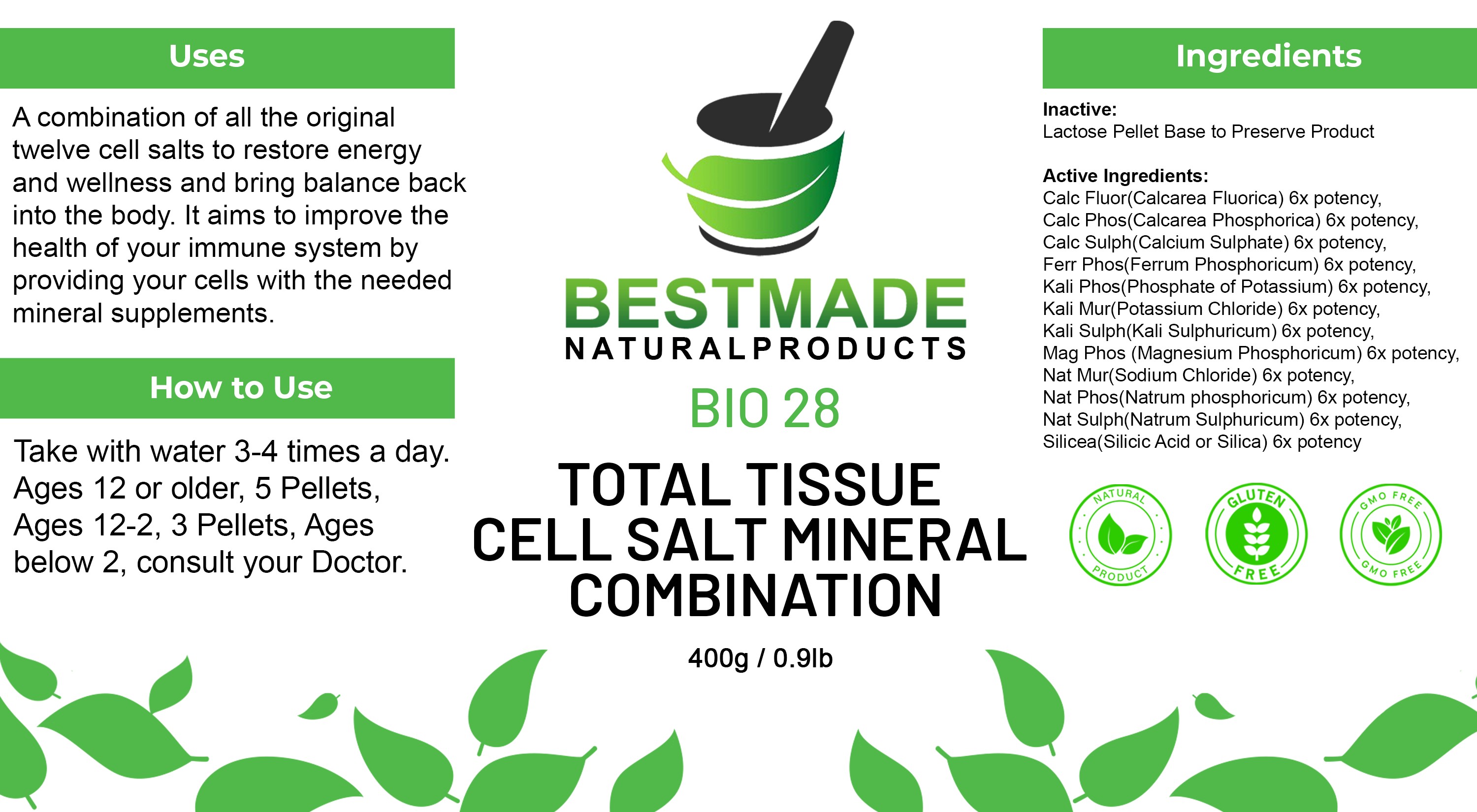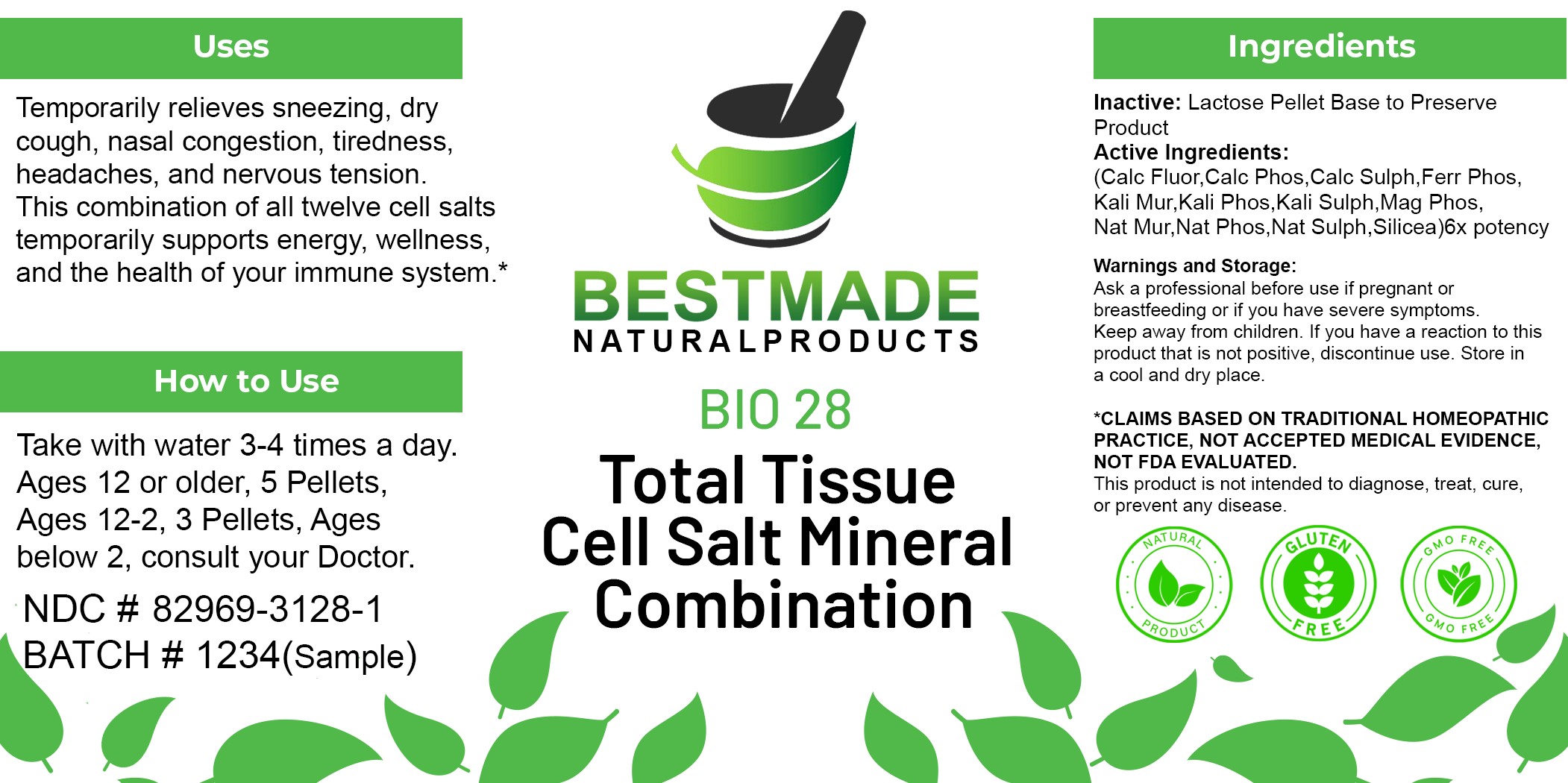 DRUG LABEL: Bestmade Natural Products BIO28
NDC: 82969-3128 | Form: GLOBULE
Manufacturer: Total Operations Management LLC DBA: Bestmade Natural Products Micro
Category: homeopathic | Type: HUMAN OTC DRUG LABEL
Date: 20251202

ACTIVE INGREDIENTS: SODIUM CHLORIDE 6 [hp_X]/1 g; SODIUM SULFATE 6 [hp_X]/1 g; CALCIUM FLUORIDE 6 [hp_X]/1 g; FERROSOFERRIC PHOSPHATE 6 [hp_X]/1 g; CALCIUM SULFATE ANHYDROUS 6 [hp_X]/1 g; SODIUM PHOSPHATE, DIBASIC, HEPTAHYDRATE 6 [hp_X]/1 g; POTASSIUM SULFATE 6 [hp_X]/1 g; TRIBASIC CALCIUM PHOSPHATE 6 [hp_X]/1 g; SILICON DIOXIDE 6 [hp_X]/1 g; MAGNESIUM PHOSPHATE, DIBASIC TRIHYDRATE 6 [hp_X]/1 g; POTASSIUM CHLORIDE 6 [hp_X]/1 g; POTASSIUM PHOSPHATE, DIBASIC 6 [hp_X]/1 g
INACTIVE INGREDIENTS: LACTOSE, UNSPECIFIED FORM 0.978 g/1 g; MAGNESIUM STEARATE 0.0208 g/1 g

BNP BIO 28 (LACTOSE)

INDICATIONS AND USAGE

Uses: Temporarily relieves sneezing, dry cough, nasal congestion, tiredness, headaches, and nervous tension. This combination of all twelve cell salts temporarily supports energy, wellness, and the health of your immune system.*

DOSAGE AND ADMINISTRATION

How to Use: Take with water 3-4 times a day. Ages 12 or older, 5 Pellets, Ages 12-2, 3 Pellets, Ages below 2, consult your Doctor.

ACTIVE INGREDIENT

Active Ingredients: (Calc Fluor, Calc Phos, Calc Sulph, Ferr Phos, Kali Mur, Kali Phos, Kali Sulph, Mag Phos, Nat Mur, Nat Phos, Nat Sulph, Silicea) 6x potency

Ingredients: Inactive: Lactose Pellet Base to Preserve Product

PURPOSE

Uses: Temporarily relieves sneezing, dry cough, nasal congestion, tiredness, headaches, and nervous tension. This combination of all twelve cell salts temporarily supports energy, wellness, and the health of your immune system.*

KEEP OUT OF REACH OF CHILDREN

Warnings and Storage: Ask a professional before use if pregnant or breastfeeding or if you have severe symptoms. Keep away from children. If you have a reaction to this product that is not positive, discontinue use. Store in a cool and dry place.

WARNINGS

Warnings and Storage: Ask a professional before use if pregnant or breastfeeding or if you have severe symptoms. Keep away from children. If you have a reaction to this product that is not positive, discontinue use. Store in a cool and dry place.

*CLAIMS BASED ON TRADITIONAL HOMEOPATHIC PRACTICE, NOT ACCEPTED MEDICAL EVIDENCE, NOT FDA EVALUATED. This product is not intended to diagnose, treat, cure, or prevent any disease.

Package 1 (30g)

Package 2 (400g)